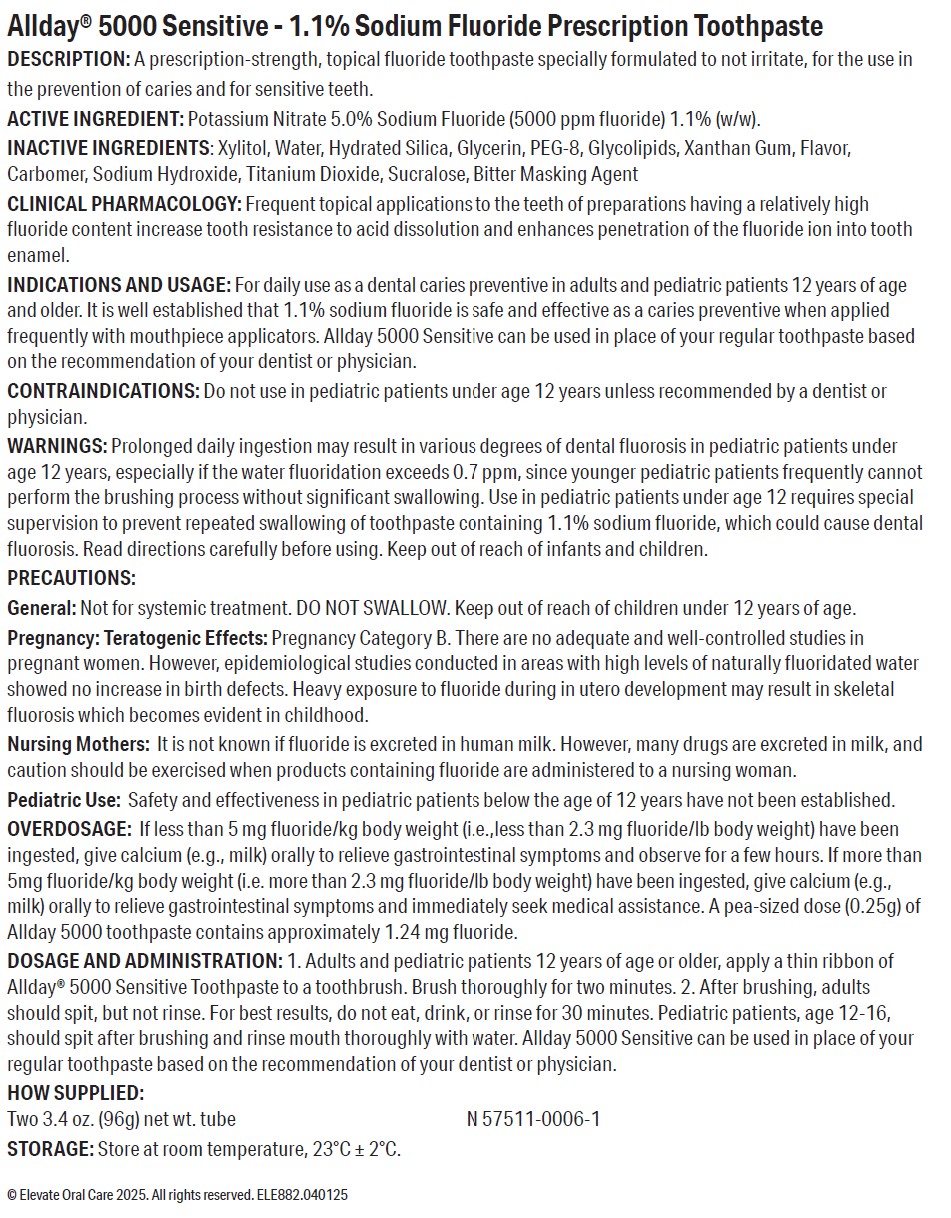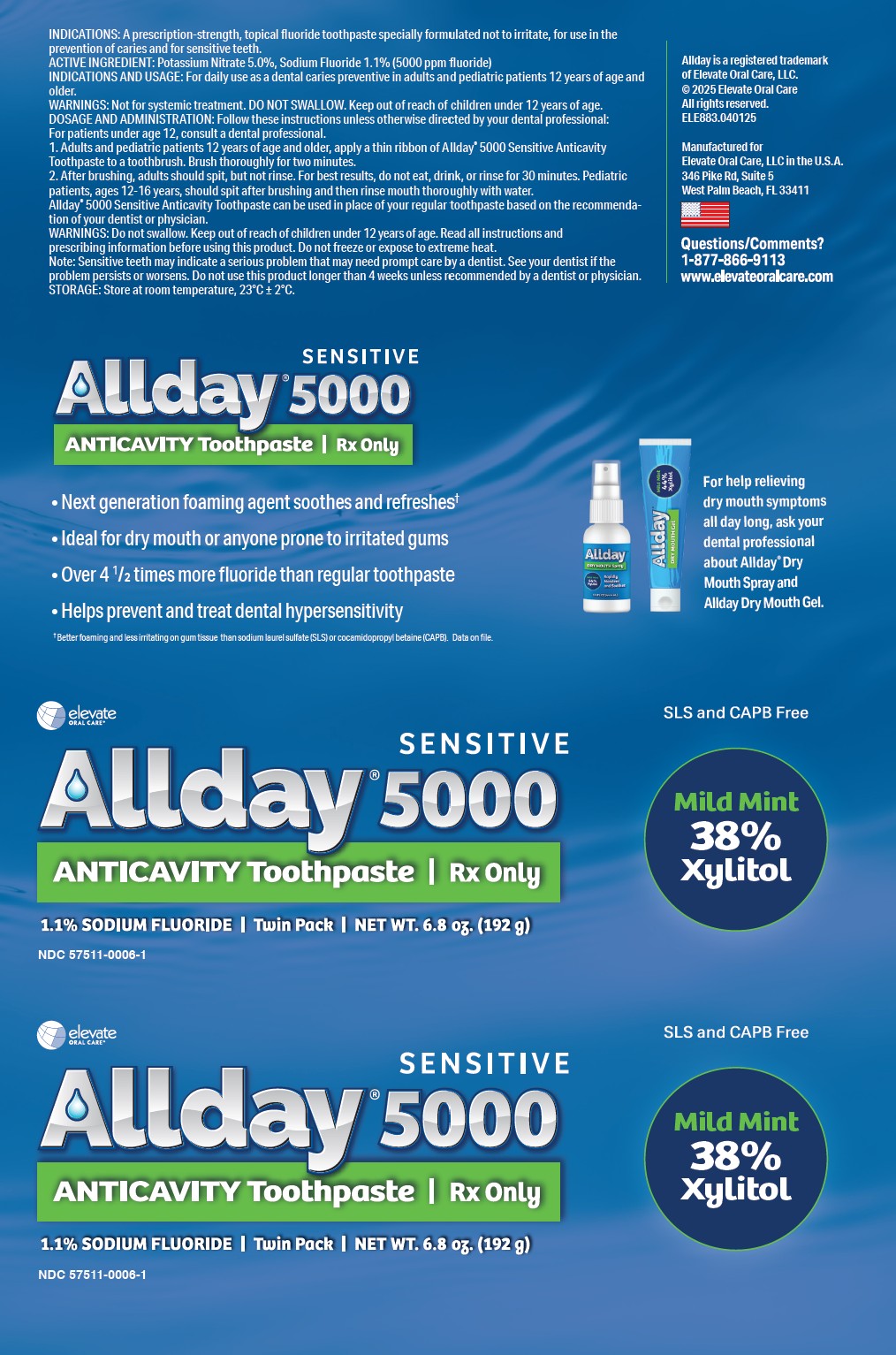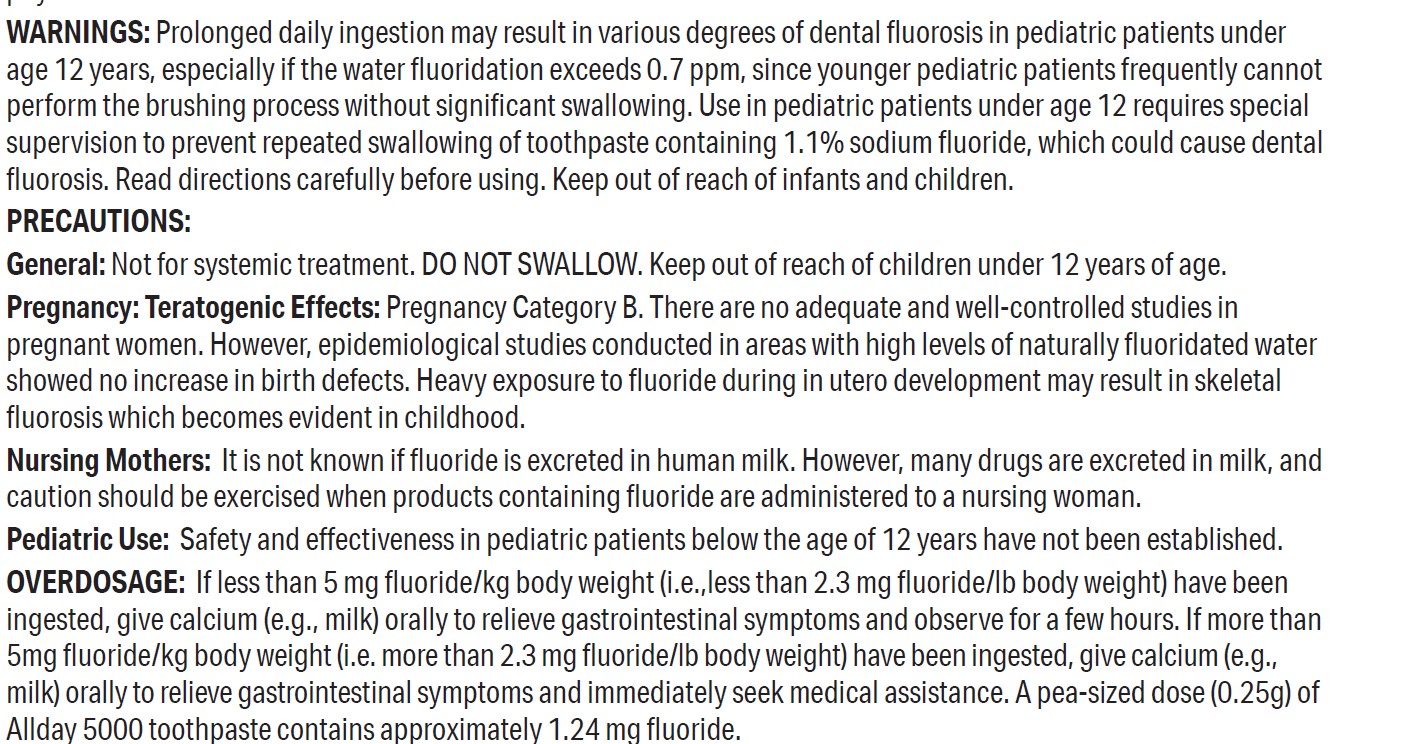 DRUG LABEL: Allday 5000 Sensitive
NDC: 57511-0006 | Form: PASTE, DENTIFRICE
Manufacturer: Elevate Oral Care
Category: prescription | Type: HUMAN PRESCRIPTION DRUG LABEL
Date: 20251112

ACTIVE INGREDIENTS: POTASSIUM NITRATE 5 g/100 g; SODIUM FLUORIDE 1.1 g/100 g
INACTIVE INGREDIENTS: GLYCERIN; HYDRATED SILICA; XYLITOL; MINT; XANTHAN GUM; SODIUM HYDROXIDE; SUCRALOSE; POLYETHYLENE GLYCOL 400; CARBOMER HOMOPOLYMER TYPE B (ALLYL PENTAERYTHRITOL CROSSLINKED); WATER; TITANIUM DIOXIDE

Allday 5000 Sensitive